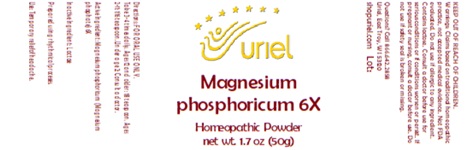 DRUG LABEL: Magnesium phosphoricum 6X
NDC: 48951-7220 | Form: POWDER
Manufacturer: Uriel Pharmacy, Inc
Category: homeopathic | Type: HUMAN OTC DRUG LABEL
Date: 20250606

ACTIVE INGREDIENTS: MAGNESIUM PHOSPHATE 6 [hp_X]/1 g
INACTIVE INGREDIENTS: LACTOSE

Magnesium phosphoricum 6X

INDICATIONS AND USAGE

Directions: FOR ORAL USE ONLY.

DOSAGE AND ADMINISTRATION

Take 3-4 times daily. Ages 12 and older: 1/8 teaspoon. Ages 2-11: 1/16 teaspoon. Under age 2: Consult a doctor.

Active Ingredient: Magnesium phosphoricum (Magnesium phosphate) 6X

Inactive Ingredient: Lactose

Prepared using rhythmical processes.

PURPOSE

Use: Temporary relief of headache.

KEEP OUT OF REACH OF CHILDREN.

WARNINGS

Warnings: Claims based on traditional homeopathic practice, not accepted medical evidence. Not FDA evaluated. Do not use if allergic to any ingredient. Contains lactose. Consult a doctor before use for serious conditions or if conditions worsen or persist. If pregnant or nursing, consult a doctor before use. Do not use if safety seal is broken or missing.

Questions? Call 866.642.2858
Uriel, East Troy, WI 53120
shopuriel.com Lot: